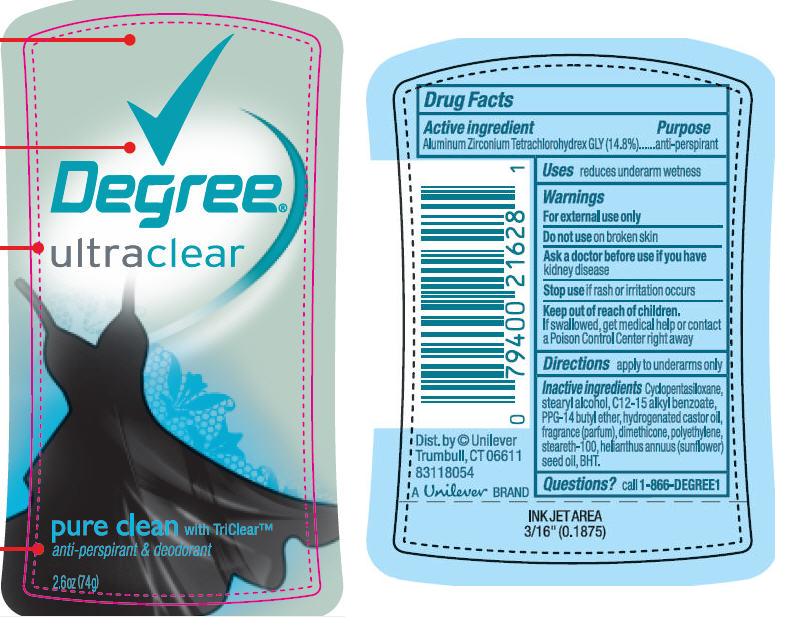 DRUG LABEL: Degree
NDC: 64942-0824 | Form: STICK
Manufacturer: Conopco Inc. d/b/a Unilever
Category: otc | Type: HUMAN OTC DRUG LABEL
Date: 20110126

ACTIVE INGREDIENTS: Aluminum Zirconium  Tetrachlorohydrex GLY 14.8 g/100 g
INACTIVE INGREDIENTS: CYCLOMETHICONE 5; STEARYL ALCOHOL; C12-15 ALKYL BENZOATE; PPG-14 BUTYL ETHER; HYDROGENATED CASTOR OIL; DIMETHICONE; STEARETH-100; SUNFLOWER OIL; BUTYLATED HYDROXYTOLUENE

Degree Ultraclear Pure Clean Antiperspirant Deodorant

Active Ingredient
Aluminum Zirconium Tetrachlorohydrex GLY (14.8%)

Purpose
anti-perspirant

Uses
reduces underarm wetness

Warnings
For external use only

Do not use on broken skin

Ask a doctor before use if you have kidney disease

Stop use if rash or irritation occurs

Keep out of reach of children. If swallowed, get medical help or contact a Poison Control Center right away

Directions
apply to underarms only

INACTIVE INGREDIENT

Cyclopentasiloxane, Stearyl Alcohol, C12-15 Alkyl Benzoate, PPG-14 Butyl Ether, Hydrogenated Castor Oil, Fragrance (Parfum), Dimethicone, Polyethylene, Steareth-100, Helianthus Annuus (Sunflower) Seed Oil, BHT

Questions? call 1-866 DEGREE1

PACKAGE LABEL

PDP 2.6 oz